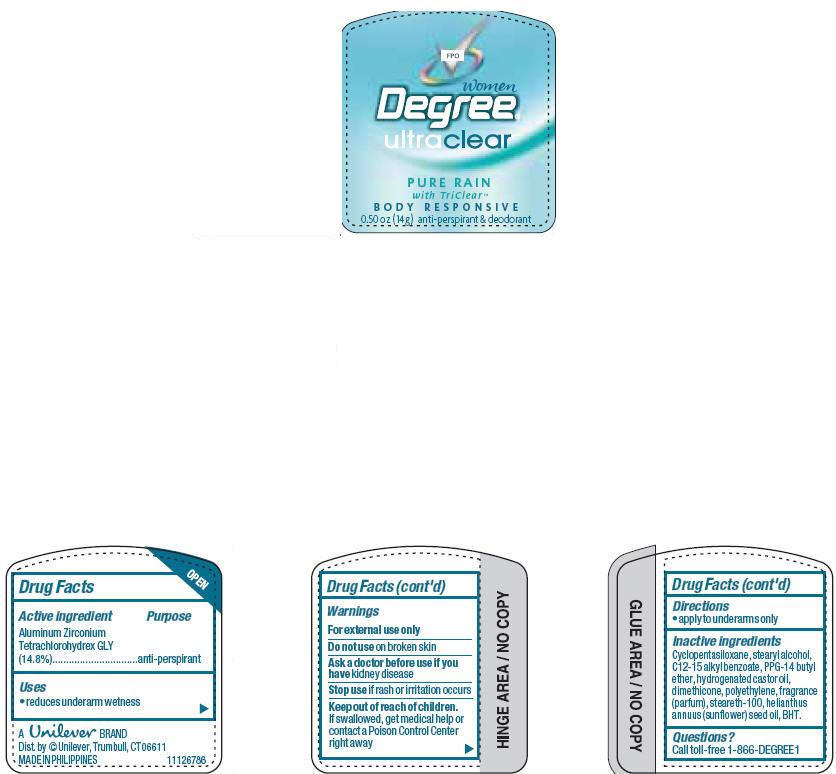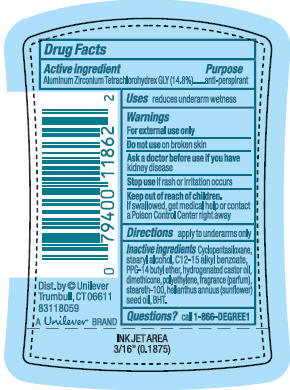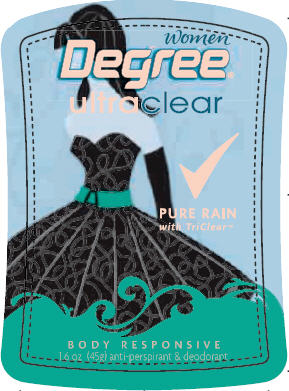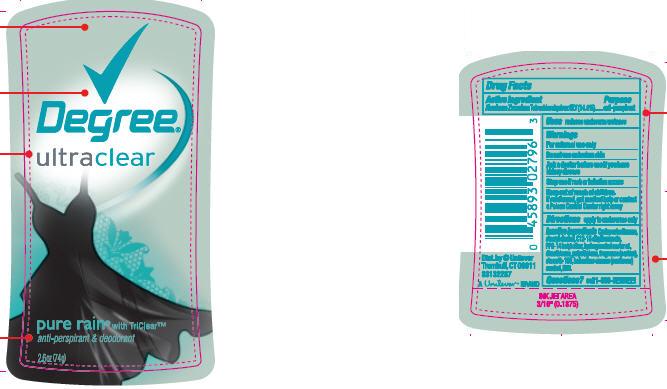 DRUG LABEL: Degree Women UltraClear Pure Rain
NDC: 64942-0782 | Form: STICK
Manufacturer: Conopco Inc. d/b/a Unilever
Category: otc | Type: HUMAN OTC DRUG LABEL
Date: 20100202

ACTIVE INGREDIENTS: Aluminum Zirconium  Tetrachlorohydrex GLY 14.8 g/100 g

Degree Women UltraClear Pure Rain AP and Deodorant PDP and drug facts

Active Ingredient Purpose
Aluminum Zirconium Tetrachlorohydrex GLY (14.8%).....anti-perspirant

Warnings
For external use only

Do not use on broken skin

Ask a doctor before use if you have kidney disease

Stop use if rash or irritation occurs

Keep out of reach of children. If swallowed, get medical help or contact a Poison Control Center right away

INACTIVE INGREDIENT

Cyclopentasiloxane, Stearyl Alcohol, C12-15 Alkyl Benzoate, PPG-14 Butyl Ether, Hydrogenated Castor Oil, Dimethicone, Polyethylene, Fragrance (Parfum), Steareth-100, Helianthus Annuus (Sunflower) Seed Oil, BHT.

Questions? call 1-866 DEGREE1

PACKAGE LABEL

PDP 2.6 oz

PACKAGE LABEL

PDP 1.6 oz front

PACKAGE LABEL

PDP 1.6 oz back

PACKAGE LABEL

0.5oz PDP